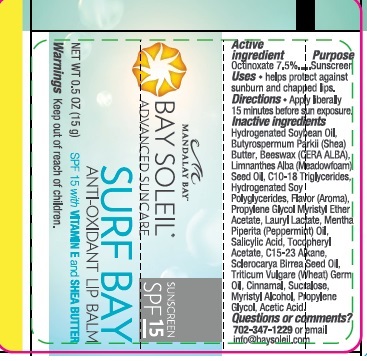 DRUG LABEL: Surf Bay Lip Balm
NDC: 61531-100 | Form: GEL
Manufacturer: Universal Packaging Systems, Inc. DBA: PakLab
Category: otc | Type: HUMAN OTC DRUG LABEL
Date: 20150925

ACTIVE INGREDIENTS: OCTINOXATE 0.075 g/1 g
INACTIVE INGREDIENTS: .ALPHA.-TOCOPHEROL ACETATE

ACTIVE INGREDIENT

Octinoxate 7.5%

PURPOSE

Help protect again sunburn and chapped lips

Warnings: Keep out of reach of children

INSTRUCTIONS FOR USE

Apply liberaly 15 minutes before sun exposure

INACTIVE INGREDIENT

Hydrogenated Soybean Oil, Butyrospermum Parkii (Shea) Butter, Beeswax (CERA ALBA), Limnanthes Alba (Meadowfoam) Seed Oil, C10-18 Triglycerides, Hydrogenated Soy Polyglycerides, Flavor (Aroma), Propylene Glycol Myristyl Ether Acetate, Lauryl Lactate, Mentha Piperita (Peppermint) Oil, Salicylic Acid, Tocopheryl Acetate, C15-23 Alkane,

Sclerocarya Birrea Seed Oil, Triticum Vulgare (Wheat) Germ Oil, Cinnamal, Sucralose, Myristyl Alcohol, Propylene Glycol, Acetic Acid.

Questions or Comments? 702-347-1229 or email info@baysoleil.com

Keep out of reach of children

INDICATIONS AND USAGE

Helps protect against sunburn and chapped lips

DOSAGE AND ADMINISTRATION

Topical gel